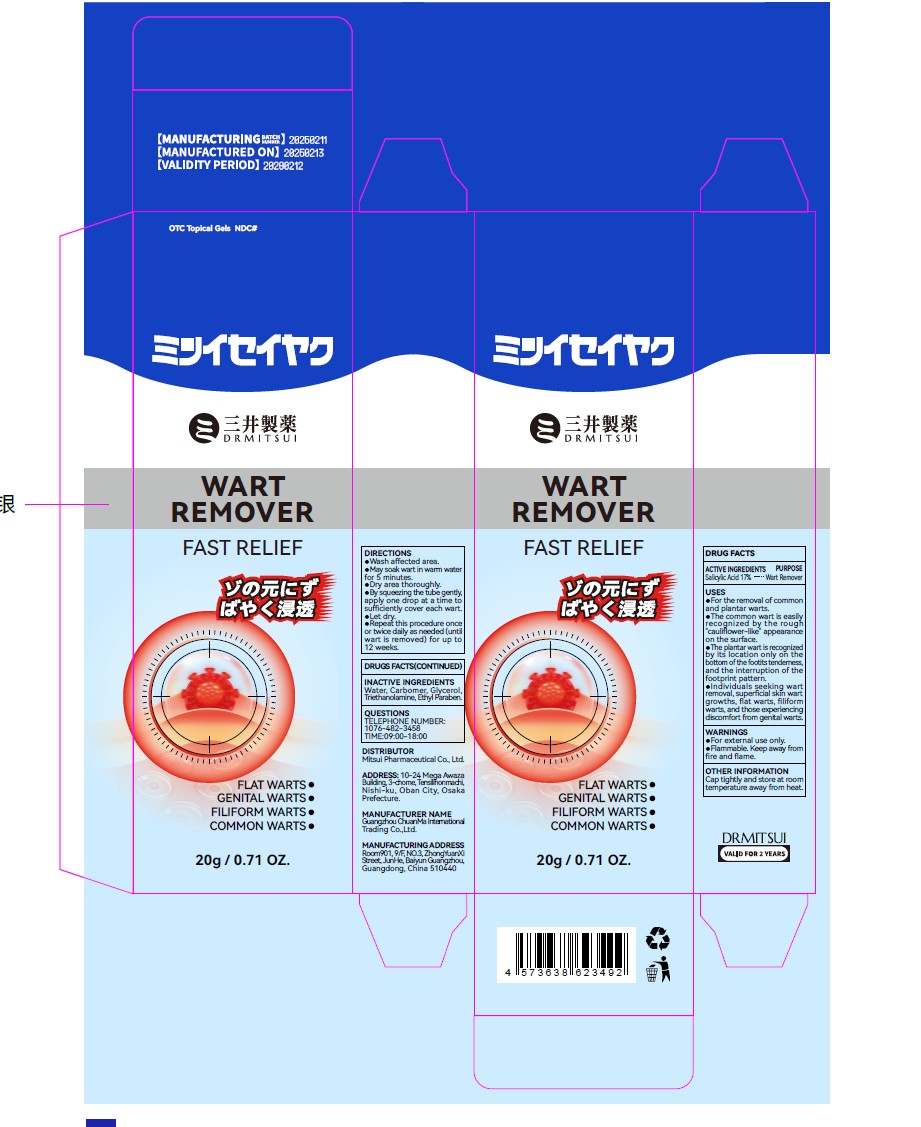 DRUG LABEL: DRMITSUI WART REMOVER
NDC: 85593-118 | Form: LIQUID
Manufacturer: Guangzhou ChuanMa International Trading Co.,Ltd.
Category: otc | Type: HUMAN OTC DRUG LABEL
Date: 20260301

ACTIVE INGREDIENTS: SALICYLIC ACID 17 g/100 g
INACTIVE INGREDIENTS: GLYCERIN; ETHYLPARABEN; WATER; TRIETHANOLAMINE; CARBOMER

85593-118-01DRMITSUI WART REMOVER

ACTIVE INGREDIENTS PURPOSE

Salicylic Acid 17%.--...Wart Remover

PURPOSE

FLAT WARTS

GENITAL WARTS

FILIFORM WARTS

COMMON WARTS

keep out of reach children

WARNINGS
For external use only.frammable. Keep away from

INDICATIONS AND USAGE

For the removal of commonand plantar warts.The common wart is easilyrecognized by the rough"cauliflower-like” appearanceon the surface.The plantar wart is recognizedby its location only on thebottom of the footits tenderness,and the interruption of thefootprint pattern.Individuals seeking wartremoval, superficial skin wartgrowths, flat warts, filiformstoto genians

DOSAGE AND ADMINISTRATION

Wash affected area.May soak wart in warm waterfor 5 minutes.

Dry area thoroughly.appureopateentdsufficiently cover each wart.

Let dry.oree hi arnecder oncwart is removed) for up to12 weeks.

INACTIVE INGREDIENTS

Water, Carbomer, Glycerol,Triethanolamine, Ethyl Paraben.